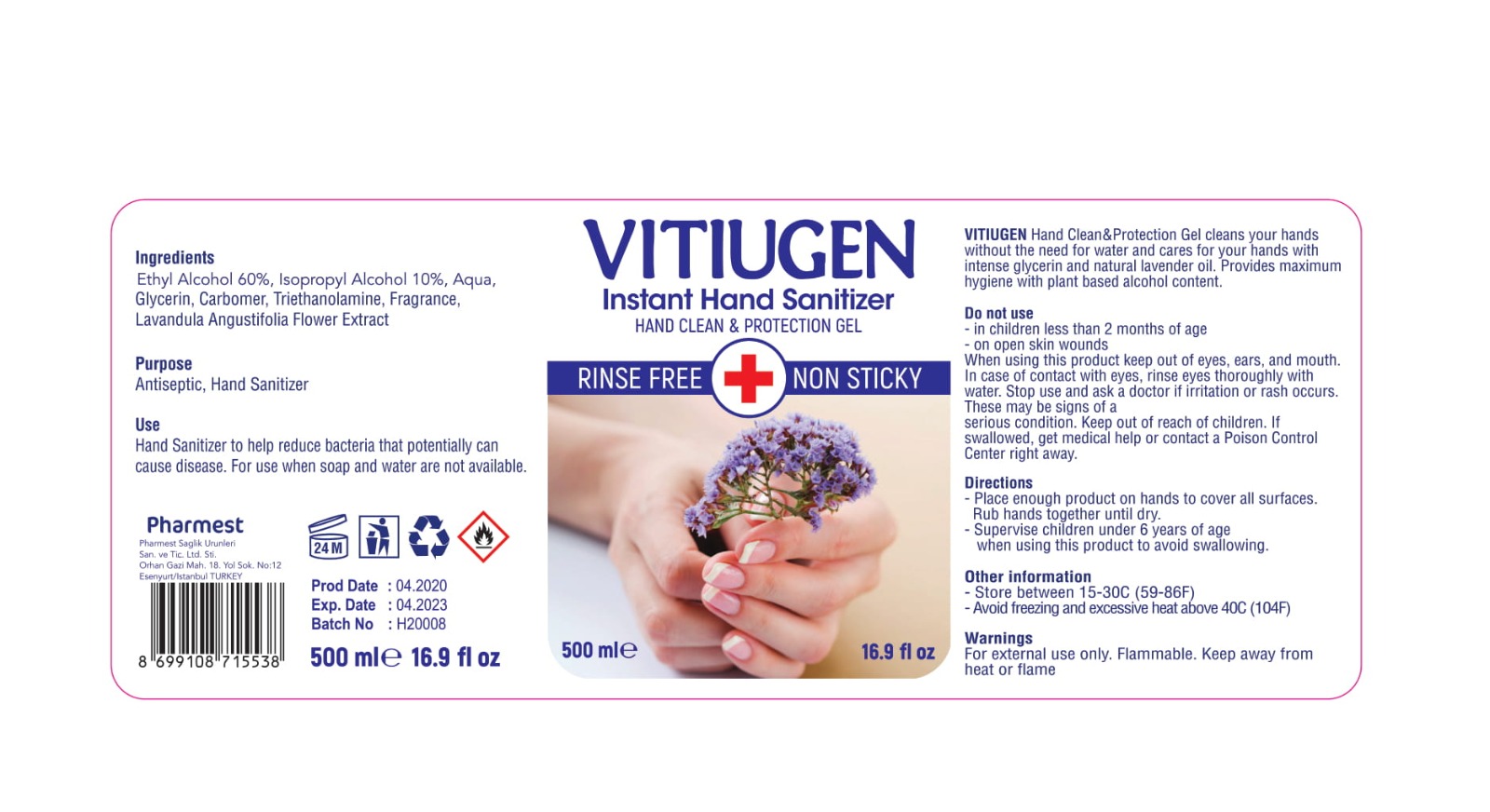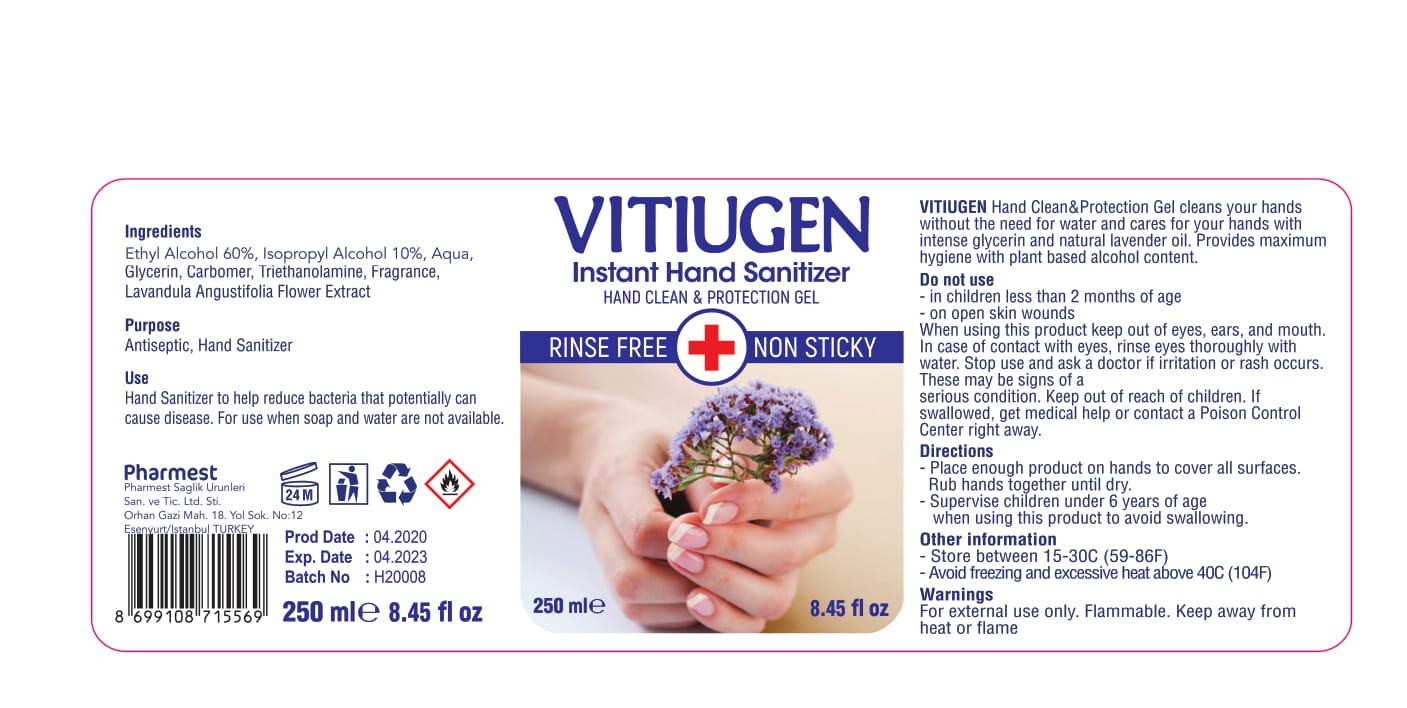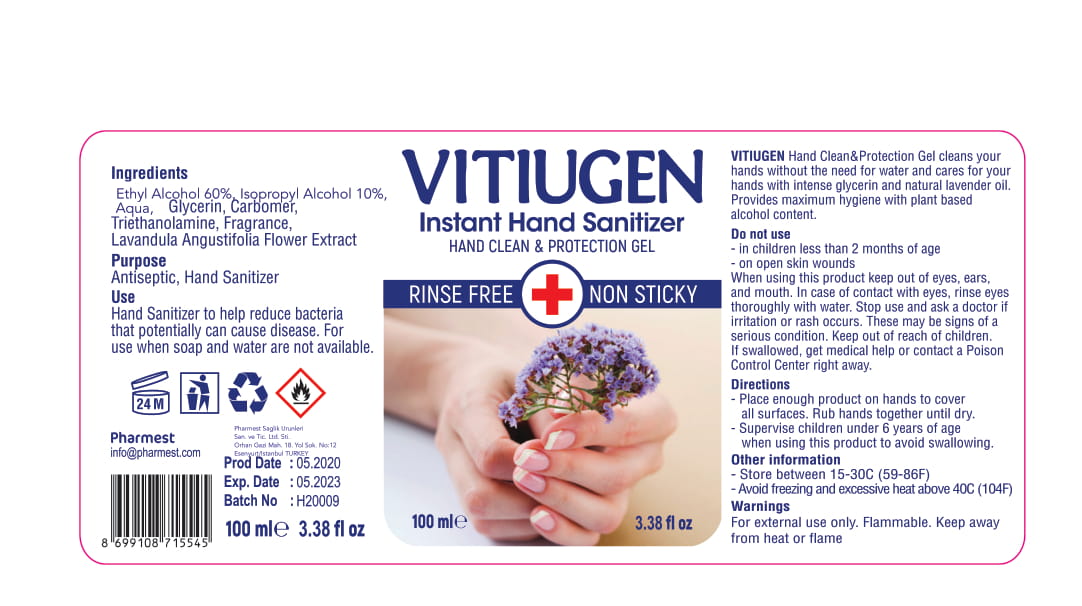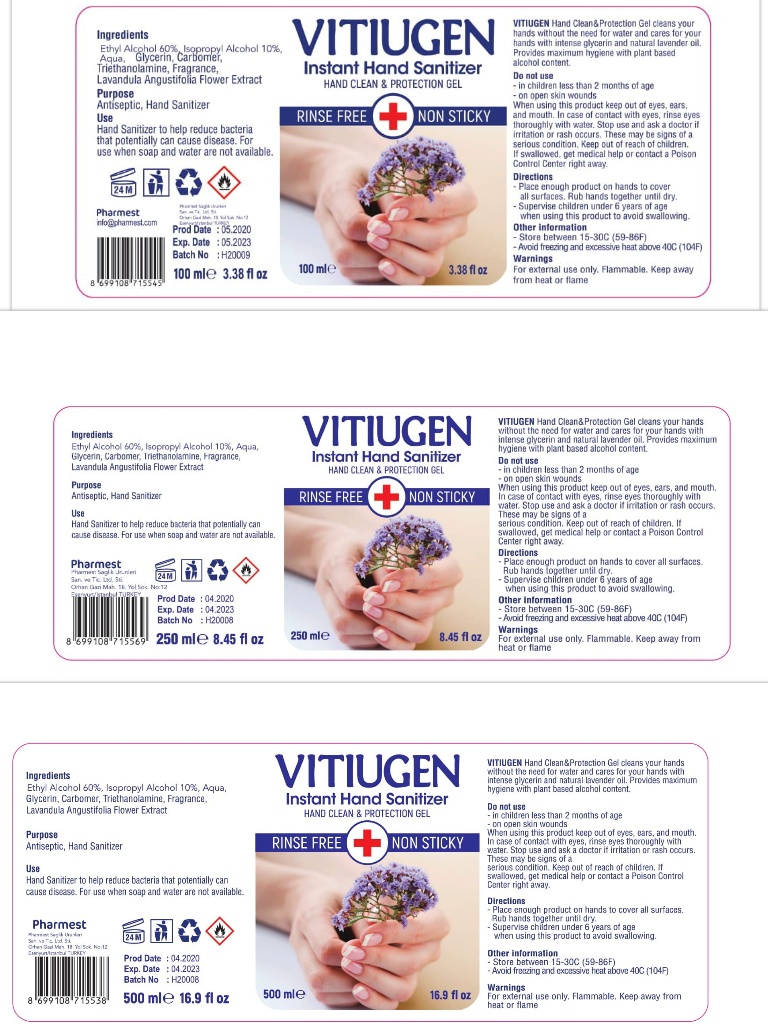 DRUG LABEL: Vitiugen Instant Hand Sanitizer
NDC: 78984-001 | Form: GEL
Manufacturer: PHARMEST SAGLIK URUNLERI SANAYI VE TICARET LIMITED SIRKETI
Category: otc | Type: HUMAN OTC DRUG LABEL
Date: 20200618

ACTIVE INGREDIENTS: ISOPROPYL ALCOHOL 10 mL/100 mL; ALCOHOL 60 mL/100 mL
INACTIVE INGREDIENTS: GLYCERIN; WATER; LAVANDULA ANGUSTIFOLIA FLOWERING TOP; CARBOMER HOMOPOLYMER, UNSPECIFIED TYPE; TROLAMINE

Active Ingredient(s)

Ethyl Alcohol 60%, Isopropyl Alcohol 10%

Purpose

Antiseptic, Hand Sanitizer

Use

Hand Sanitizer to help reduce bacteria that potentially can cause disease. For use when soap and water are not available.

Warnings

For external use only. Flammable. Keep away from heat or flame

Do not use

- in children less than 2 months of age
- on open skin wounds

When using this product keep out of eyes, ears, and mouth. In case of contact with eyes, rinse eyes thoroughly with water.
Stop use and ask a doctor if irritation or rash occurs. These may be signs of a serious condition.
Keep out of reach of children. If swallowed, get medical help or contact a Poison Control Center right away.

Stop use and ask a doctor if irritation or rash occurs. These may be signs of a serious condition.

Keep out of reach of children. If swallowed, get medical help or contact a Poison Control Center right away.

Directions

- Place enough product on hands to cover all surfaces. Rub hands together until dry.
- Supervise children under 6 years of age when using this product to avoid swallowing.

Other information

- Store between 15-30C (59-86F)
- Avoid freezing and excessive heat above 40C (104F)

Inactive ingredients

Glycerin, Carbomer, Triethanolamine, Fragrance, Lavandula Angustifolia Flower Extract

PACKAGE LABEL

Pharmest

Prod. date: 04.2020

Exp. date: 04.2023

Batch No: H20008

Vitiugen Instant Hand Sanitizer

Hand Clean & Protection Gel

Rinse Free

Non Sticky

Pharmest Saglik Urunleri

San. ve Tic. Ltd. Sti.

Orhan Gazi Mah. 18. Yol Sok. No:12

Esenyurt/Istanbul TURKEY